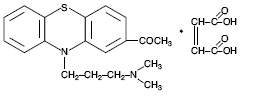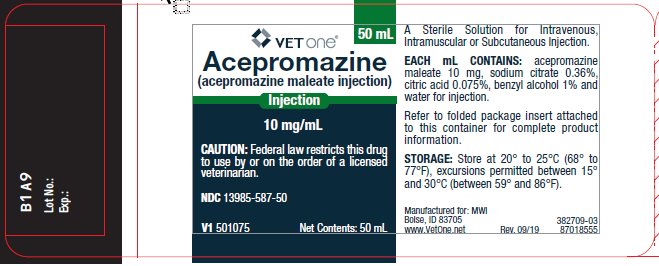 DRUG LABEL: Acepromazine maleate
NDC: 13985-587 | Form: INJECTION
Manufacturer: MWI/VetOne
Category: animal | Type: PRESCRIPTION ANIMAL DRUG LABEL
Date: 20250423

ACTIVE INGREDIENTS: ACEPROMAZINE MALEATE 10 mg/1 mL
INACTIVE INGREDIENTS: BENZYL ALCOHOL 10 mg/1 mL; TRISODIUM CITRATE DIHYDRATE 3.6 mg/1 mL; ANHYDROUS CITRIC ACID 0.75 mg/1 mL; WATER

Acepromazine Injection
(acepromazine maleate injection)

Approved by FDA under NADA # 015-030

Caution:

Federal law restricts this drug to use by or on the order of a licensed veterinarian.

Description:

Acepromazine Injection, a potent neuroleptic agent with a low order of toxicity, is of particular value in the tranquilization of dogs, cats and horses. Its rapid action and lack of hypnotic effect are added advantages. According to Baker,^1 the scope of possible applications for this compound in veterinary practice is only limited by the imagination of the practitioner.

Each mL contains: acepromazine maleate 10 mg, sodium citrate 0.36%, citric acid 0.075%, benzyl alcohol 1% and water for injection.

Acepromazine [10-[3-(dimethyl-amino) propyl] phenothiazin-2-yl-methyl ketone] Maleate, USP has the following chemical structure:

Acepromazine Injection has a depressant effect on the central nervous system and, therefore, causes sedation, muscular relaxation and a reduction in spontaneous activity. It acts rapidly, exerting a prompt and pronounced calming effect.

Indications:

Dogs and Cats: Acepromazine Injection can be used as an aid in controlling intractable animals during examination, treatment, grooming, x-ray and minor surgical procedures; to alleviate itching as a result of skin irritation; as an antiemetic to control vomiting associated with motion sickness.

Acepromazine Injection is particularly useful as a preanesthetic agent (1) to enhance and prolong the effects of barbiturates, thus reducing the requirements for general anesthesia; (2) as an adjunct to surgery under local anesthesia.

Horses: Acepromazine Injection can be used as an aid in controlling fractious animals during examination, treatment, loading and transportation. Particularly useful when used in conjunction with local anesthesia for firing, castration, neurectomy, removal of skin tumors, ocular surgery and applying casts.

Dosage and Administration:

The dosage should be individualized, depending upon the degree of tranquilization required. As a general rule, the dosage requirement in mg/lb of body weight decreases as the weight of the animal increases.

Acepromazine Injection may be given intravenously, intramuscularly or subcutaneously. The following schedule may be used as a guide to IV, IM or SC injections:

Dogs: 0.25–0.5 mg/lb of body weight
  Cats: 0.5–1 mg/lb of body weight
  Horses: 2–4 mg/100 lb of body weight

IV doses should be administered slowly, and a period of at least 15 minutes should be allowed for the drug to take full effect.

Contraindications:

Phenothiazines may potentiate the toxicity of organophosphates and the activity of procaine hydrochloride. Therefore, do not use Acepromazine Injection (acepromazine maleate injection) to control tremors associated with organic phosphate poisoning. Do not use in conjunction with organophosphorus vermifuges or ectoparasiticides, including flea collars. Do not use with procaine hydrochloride.

Warning:

Do not use in horses intended for human consumption.

Precautions:

Tranquilizers are potent central nervous system depressants and they can cause marked sedation with suppression of the sympathetic nervous system.

Tranquilizers can produce prolonged depression or motor restlessness when given in excessive amounts or when given to sensitive animals.

Tranquilizers are additive in action to the actions of other depressants and will potentiate general anesthesia. Tranquilizers should be administered in smaller doses and with greater care during general anesthesia and also to animals exhibiting symptoms of stress, debilitation, cardiac disease, sympathetic blockade, hypovolemia or shock. Acepromazine Injection, like other phenothiazine derivatives, is detoxified in the liver; therefore, it should be used with caution in animals with a previous history of liver dysfunction or leukopenia.

Hypotension can occur after rapid intravenous injection causing cardiovascular collapse.

Epinephrine is contraindicated for treatment of acute hypotension produced by phenothiazine-derivative tranquilizers since further depression of blood pressure can occur. Other pressor amines, such as norepinephrine or phenylephrine, are the drugs of choice.

In horses, paralysis of the retractor penis muscle has been associated with the use of phenothiazine-derivative tranquilizers. Such cases have occurred following the use of Acepromazine Injection. This risk should be duly considered prior to the administration of Acepromazine Injection to male horses (castrated and uncastrated). When given, the dosage should be carefully limited to the minimum necessary for the desired effect. At the time of tranquilization, it is not possible to differentiate between reversible protrusion of the penis (a normal clinical sign of narcosis) and the irreversible paralysis of the retractor muscle. The cause of this side reaction has not been determined. It has been postulated that such paralysis may occur when a tranquilizer is used in conjunction with testosterone (or in stallions).

Accidental intracarotid injection in horses can produce clinical signs ranging from disorientation to convulsive seizures and death.

Adverse Reactions:

A few rare but serious occurrences of idiosyncratic reactions to acepromazine may occur in dogs following oral or parenteral administration. These potentially serious adverse reactions include behavioral disorders in dogs such as aggression, biting/chewing, and nervousness.

To report suspected adverse reactions, to obtain a Safety Data Sheet or for technical assistance, call 1-888-637-4251. For additional information about adverse drug experience reporting for animal drugs, contact FDA at 1-888-FDA-VETS, or www.fda.gov/reportanimalae.

Animal Safety:

Acute and chronic toxicity studies have shown a very low order of toxicity.

Acute toxicity: The LD50 dose of Acepromazine Injection in mice was determined by means of a probit transformation with the following results:^2

Intravenous route — 61.37 mg/kg
  Subcutaneous route — 130.5 mg/kg
  Oral route — 256.8 mg/kg

Chronic toxicity: Tests^3 in rats revealed no deleterious effects on renal or hepatic function or on hemopoietic activity. In several groups of two male and two female beagle hounds treated for six months with daily oral doses of 20 to 40 mg/kg, no untoward effects were encountered. Hematologic studies and urinalysis gave values within normal limits. Another group of four dogs, given gradually increasing oral doses up to a level of 220 mg/kg daily and reaching a total daily dose of 2.2 g per dog, showed some signs of pulmonary edema and hyperemia of the internal organs, but no animal died.

When administered intramuscularly, Acepromazine Injection causes a brief sensation of stinging comparable with that observed with other phenothiazine tranquilizers.

Effectiveness:

Controlled clinical studies in the United States and Canada have demonstrated the effectiveness and safety of Acepromazine Injection as a tranquilizer.

Good to excellent results were reported^1,4,5 in dogs, cats and horses given Acepromazine Injection for restraint during examination, treatment and minor surgery and for preanesthetic sedation. In dogs, the drug reportedly^4 helps control convulsions associated with distemper.

In both dogs and cats, good to excellent results were obtained^4 when Acepromazine Tablets were used to control nervousness, excessive vocalization, neurotic and excitable behavior, vomiting associated with motion sickness, coughing and itching caused by dermatitis.

In horses, Bauman^6 had good results using the drug as an aid in the control of painful spasms due to colic.

Other practitioners^7,8 found the drug useful as a preanesthetic sedative for nervous or aggressive horses, but it had to be administered while the animals were quiet and not in an excited state. In a trial^9 on more than 200 horses with a wide variety of disorders, Acepromazine Injection proved to be both effective and safe.

Storage:

Store at 20° to 25°C (68° to 77°F), excursions permitted between 15° and 30°C (between 59° and 86°F). When used as labeled, there is no limit on the number of punctures through-out the full expiry period.

How Supplied:

Acepromazine Injection is supplied in 50 mL multiple dose vials.

NDC 13985-587-50 - 10 mg/mL - 50 mL vial

References:

1. Baker, J.M.: Paper presented at the Ontario Veterinary Association meeting, held in Toronto, Canada, 1958.
2. Pharmacology Reports, ClinByla Laboratories, Paris, France.
3. Stegen, M.G.: Pharmacology Report, Ayerst Laboratories, 1958.
4. Veterinary Medical Records, Ayerst Laboratories.
5. Foley, J.T.: Clinical Reports to Ayerst Laboratories, 1963.
6. Bauman, W.G.: Clinical Reports to Ayerst Laboratories, 1963.
7. Ford, R.W.: in Equine Panel Report, Mod. Vet. Pract. 40:45 (Nov. 1) 1959.
8. Baldwin, R.: in Equine Panel Report, Mod. Vet. Pract. 40:46 (Nov. 1) 1959.
9. Dunkin, T.E.: Clinical Reports to Ayerst Laboratories, 1963.

Manufactured for: MWI

Boise, ID 83705

www.VetOne.net

Rev. 09/19